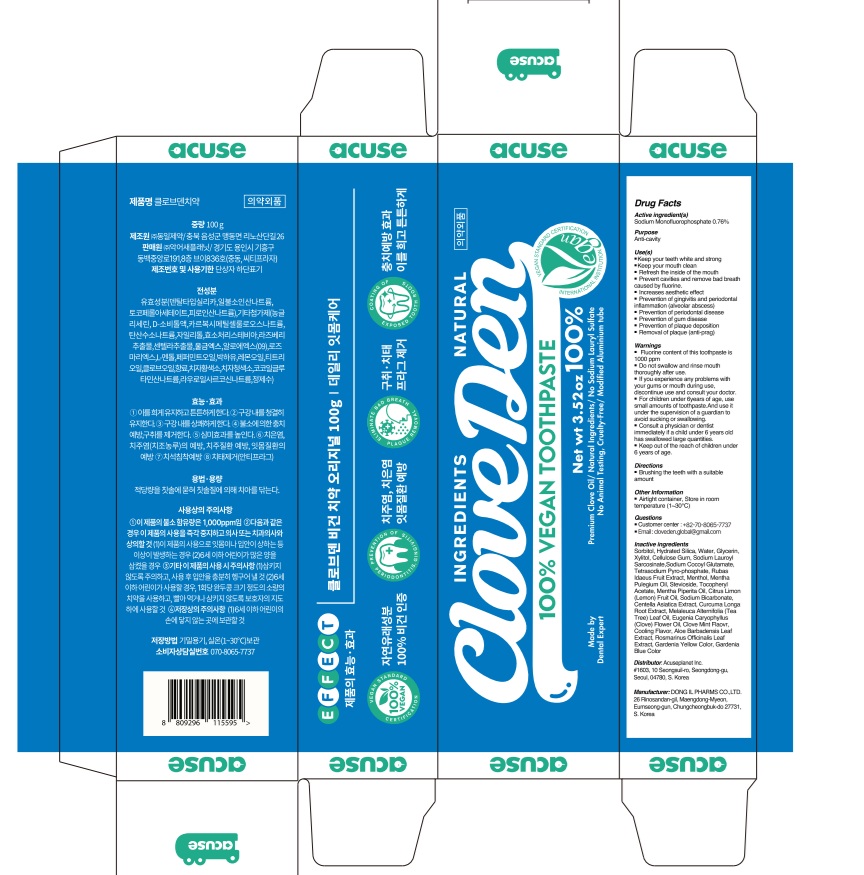 DRUG LABEL: Cloveden Tooth
NDC: 73242-1112 | Form: PASTE, DENTIFRICE
Manufacturer: DONG IL PHARMS CO.,LTD
Category: otc | Type: HUMAN OTC DRUG LABEL
Date: 20250926

ACTIVE INGREDIENTS: SODIUM MONOFLUOROPHOSPHATE 0.76 g/100 g
INACTIVE INGREDIENTS: GLYCERIN; SORBITOL; WATER

Active ingredient(s)

Sodium Monofluorophosphate 0.76%

Purpose

Anti-cavity

INDICATIONS AND USAGE

Use(s)

■ Keep your teeth white and strong

■ Keep your mouth clean

■ Refresh the inside of the mouth

■ Prevent cavities and remove bad breath caused by fluorine.

■ Increases aesthetic effect

■ Prevention of gingivitis and periodontal inflammation (alveolar abscess)

■ Prevention of periodontal disease

■ Prevention of gum disease

■ Prevention of plaque deposition

■ Removal of plaque (anti-prag)

Warnings

■ Fluorine content of this toothpaste is 1000 ppm

■ Do not swallow and rinse mouth thoroughly after use.

■ If you experience any problems with your gums or mouth during use,

discontinue use and consult your doctor.

■ For children under 6 years of age, use small amounts of toothpaste.

And use it under the supervision of a guardian to avoid sucking or swallowing.

■ Consult a physician or dentist immediately if a child under 6 years old has

swallowed large quantities.

■ Keep out of the reach of children under 6 years of age.

KEEP OUT OF REACH OF CHILDREN

■ Keep out of the reach of children under 6 years of age.

Directions

Brushing the teeth with a suitable amount

Other Information

■ Airtight container, Store in room temperature (1~30℃)

Inactive ingredients

Sorbitol, Hydrated Silica, Water, Glycerin, Xylitol, Cellulose Gum, Sodium Lauroyl Sarcosinate, Sodium Cocoyl Glutamate, Tetrasodium Pyrophosphate, Rubas Idaeus Fruit Extract, Menthol, Mentha Pulegium Oil, Stevioside, Tocopheryl Acetate, Mentha Piperita Oil, Citrus Limon (Lemon) Fruit Oil, Sodium Bicarbonate, Centella Asiatica Extract, Curcuma Longa Root Extract, Melaleuca Alternifolia (Tea Tree) Leaf Oil, Eugenia Caryophyllus (Clove) Flower Oil, Clove Mint Flaovr, Cooling Flavor, Aloe Barbadensis Leaf Extract, Rosmarinus Officinalis Leaf Extract, Gardenia Yellow Color, Gardenia Blue Color